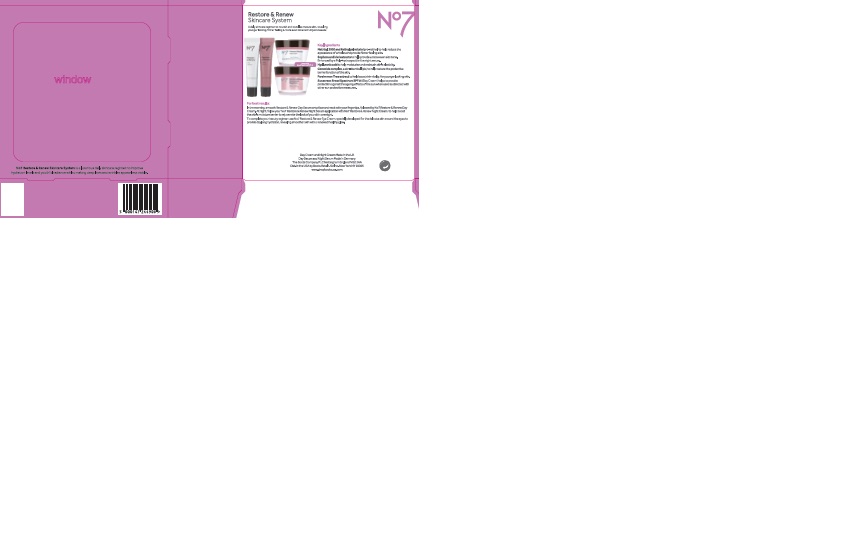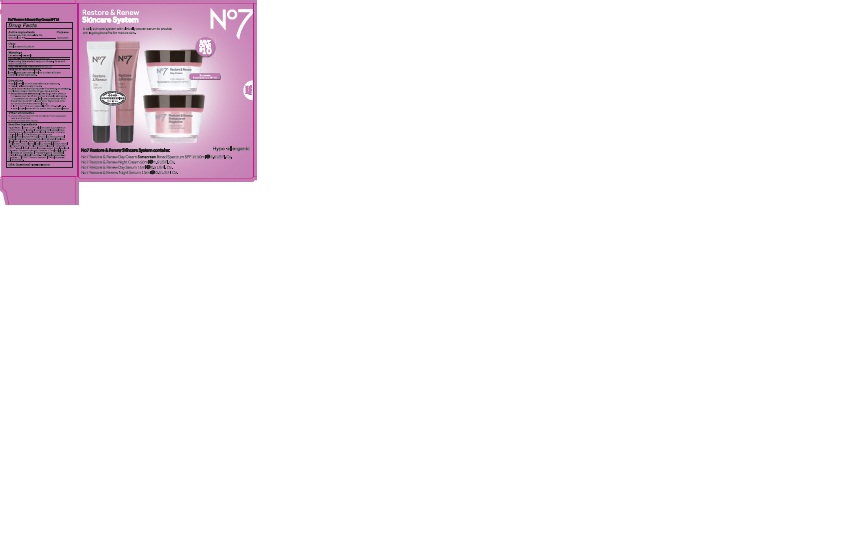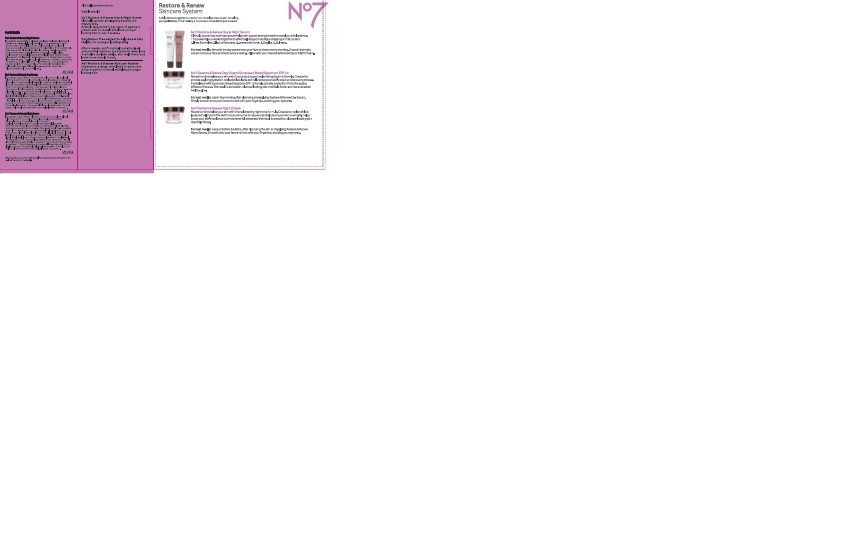 DRUG LABEL: No7 Restore and Renew Day Cream SPF 15
NDC: 11489-114 | Form: CREAM
Manufacturer: BCM Ltd
Category: otc | Type: HUMAN OTC DRUG LABEL
Date: 20161011

ACTIVE INGREDIENTS: AVOBENZONE 1.5 g/50 g; OCTOCRYLENE 2 g/50 g; OCTISALATE 1 g/50 g
INACTIVE INGREDIENTS: WATER; GLYCERIN; DIMETHICONE; ALKYL (C12-15) BENZOATE; ISOSTEARYL ISOSTEARATE; TRIBEHENIN; CYCLOMETHICONE 5; AMMONIUM ACRYLOYLDIMETHYLTAURATE/VP COPOLYMER; CYCLOMETHICONE 6; GLYCERYL STEARATE SE; PHENOXYETHANOL; CETOSTEARYL ALCOHOL; SHEA BUTTER; PEG-100 STEARATE; BUTYLENE GLYCOL; MYRISTYL MYRISTATE; ROSA CANINA FRUIT OIL; METHYLPARABEN; DIMETHICONOL (40 CST); ETHYLPARABEN; XANTHAN GUM; SODIUM LAUROYL LACTYLATE; VITAMIN A PALMITATE; ASCORBYL GLUCOSIDE; DIOSPYROS KAKI LEAF; EDETATE SODIUM; CHOLESTEROL; TERT-BUTYL ALCOHOL; LUPINUS ALBUS SEED OIL; PROPYLENE GLYCOL; POLYSORBATE 20; CARBOMER 940; POTASSIUM HYDROXIDE; ETHYLHEXYLGLYCERIN; CERAMIDE 3; CERAMIDE 6 II; TOCOPHEROL; PHYTOSPHINGOSINE; TITANIUM DIOXIDE; TRIETHYL CITRATE; PALMITOYL TETRAPEPTIDE-7; PALMITOYL TRIPEPTIDE-1; CERAMIDE 1; FD&C RED NO. 4

No7 Restore and Renew Day Cream Sunscreen Broad Spectrum SPF15

Carton Active Ingredients Section

Active ingredients

Avobenzone 3%

Octisalate 2%

Octocrylene 4%

Uses

Uses - helps prevent sunburn

Warnings

For external use only

Do not use on damaged or broken skin

When using this product keep out of eyes. Rinse with water to remove.

Ask a doctor

Stop use and ask a doctor if rash occurs

Keep out of reach of children

If swallowed, get medical help or contact a Poison Control Center right away

Directions

Apply liberally 15 minutes before sun exposure

reapply at least every 2 hours

use a water resistant sunscreen if swimming or sweating

children under 6 months of age: Ask a doctor

Sun Protection Measures. Spending time in the sun increases your risk of skin cancer and early skin aging.

To decrease this risk, regularly use a sunscreen with a Broad Spectrum SPF value of 15 or higher and other sun protection measures including:

Limit time in the sun, especially from 10 a.m - 2 p.m.

wear long-sleeved shirts,pants,hats and sunglasses.

Storage

Other information

Protect the product in this container from excessive heat and direct sun

Avoid contact with fabrics

Inactive ingredients

Aqua(Water), Glycerin, C12-15 alkyl bezoate, Butyrospermum parkii (Shea) butter, Isostearyl isostearate, Cyclopentasiloxane, Dimethicone, Cyclohexasiloxane, Glyeryl stearate, Tribehenin, Cetearyl alcohol, PEG-100 stearate, Ammonium acryloyldimethyltaurate/VP copolymer, Silica, Phenoxyethanol, Myristyl myristate, Rosa canina fruit oil, Dimethiconol, Butylene glycol, Methylparaben, Parfum(Fragrance), Xanthan gum, Ethylparaben, Sodium lauroyl lactylate, Ascorbyl glucoside, Retinyl palmitate, Diospyros kaki calyx extract, Cholesterol, Tetrasodium EDTA, T-butyl alcohol, Lupinus albus seed extract, Propylene glycol, Carbomer, Potassium hydroxide, Ceramide 3, Ethylhexylglycerin, Polysorbate 20, Ceramide 6 ll, Phytosphingosine, Tocopherol, Triethyl citrate, Palmitoyl tripeptide-1, Palmitoyl tetrapeptide-7, Ceramide 1, CI77891(Titanium dioxide) CI 77491(Iron oxides), CI14700(Red 4)

PATIENT COUNSELING INFORMATION

The Boots Company PLC Nottingham England NG2 3AA

Dist. by Boots Retail USA Inc. New York NY 10005

Made in the UK

www.boots.com

Description

No7 Restore and Renew Skincare System is a luxurious daily skincare regimen to improve hydration levels and youthful radiance whilst making deep lines and wrinkles appear less visible.

Restore and Renew Skincare System

A daily skincare regimen to nourish and revitalise mature skin, revealing younger looking, firmer feeling and more even toned skin in just 4 weeks.

Key Ingredients

Matrixyl 300 and Retinyl palmitate (pro-retinol) to help reduce the appearance of wrinkles and provide firmer feeling skin.

Sophora and kiwi extracts to help provide a more even skin tone. Enhanced by a Poly-hydroxyacid in the night serum.

Hyaluronic acid to help moisturise and maintain skin's elasticity.

Ceramide complex, a skin-identical lipid, to help restore the protective barier function of the skin.

Persimmon Tree extract to help boost skin vitality, for younger looking skin.

Sunscreen Broad Spectrum SPF 15 (Day Cream) helps to provide protection against the ageing effects of the sun when used as directed with ohter sun protection measures.

For Best results:

In the morning, smooth Restore and Renew Day Serum onto face and neck with your fingertips, followed by No7 Restore and Renew Day Crea. At night, follow your No7 Restore and Renew Night Serum application with No7 Restore and Renew Night Cream, to help boost the skin's moisture barrier

Description

Restore and Renew Skincare System

A daily skincare system with clinically proven serum to provide anti-ageing benefits for mature skin

No7 Restore and Renew Skincare System contains:

No7 Restore and Renew Day Cream Sunscreen Broad Spectrum SPF 15 50ml e 1.6 US Fl.Oz

No7 Restore and Renew Night Cream 50ml e 1.6 US Fl.Oz

No7 Restore and Renew Day Serum 15ml e 0.5 US Fl. Oz.

No7 Restore and Renew Night Serum 15ml e 0.5 US Fl.Oz.

Clinically proven serum

Visible results

No7 Restore and Renew Day and Night Serum

Clinically proven anti-ageing benefits for mature skin.

Actively targets the 5 key signs of ageing in mature skin to reveal revitalised younger looking skin in just 4 weeks.

Persimmon Tree extract to help boost skin vitality, for younger looking skin.

After 4 weeks, skin's natural hydration level and youthful radiance are improved, deep lines and wrinkles are less visible, skin feels firmer and looks more evenly toned.

No7 Restore and Renew Skincare System

Experience a range formulated to work even better together to reveal revitalised younger looking skin.

Description

Restore and Renew Skincare System

A daily skincare regimen to nourish and revitalise mature skin, revealing younger looking, firmer feeling and more evenly toned skin in just 4 weeks.

No7 Restore and Renew Day and Night Serum

Clinically proven day and night serum helps skin appear strengthened to reveal youthful radiance. This powerful duo works together to effectively target 5 key signs of ageing in mature skin: 1. lines and wrinkles, 2.lack of firmness, 3.uneven skin tone, 4.fragility, 5 dullness.

For best results: Smooth the day serum onto your face and neck every morning. Smooth the night serum onto your face and neck every evening. Follow with your Restore and Renew Day or Night Crea.

No7 Restore and Renew Day Cream Sunscreen Broad Spectrum SPF 15

Nourish and revitalise your skin with this protecting and replenishing daytime formula. Created to provide day long hydration, replenish lost lipids and help boost your skin's repair and recovery process. Formulated with Sunscreen Broad Spectrum SPF 15 to help provide protection from the ageing effects of the sun. The result is smoother, plumper looking skin that feels firmer and has a renewed healthy glow.

For best results: Use in the morning after cleansing and applying Restore and Renew Day Serum. Simply smooth onto your face and neck with your fingertips, avoiding your eye area.

No7 Restore and Renew Night Cream

Nourish and revitalise your skin with this replenishing night time formula. Created to replenish lost lipids and help boost the skin's moisture barrier to rejuvenate the look of your skin overnight. Helps boost your skin's resilience to environmental stress and the result is smoother, plumper looking skin that feels firmer.

For best results: Use just before bedtime, after cleansing the skin and applying Restore and Renew Night Serum. Smooth onto your face and neck with your fingertips, avoiding your eye area.